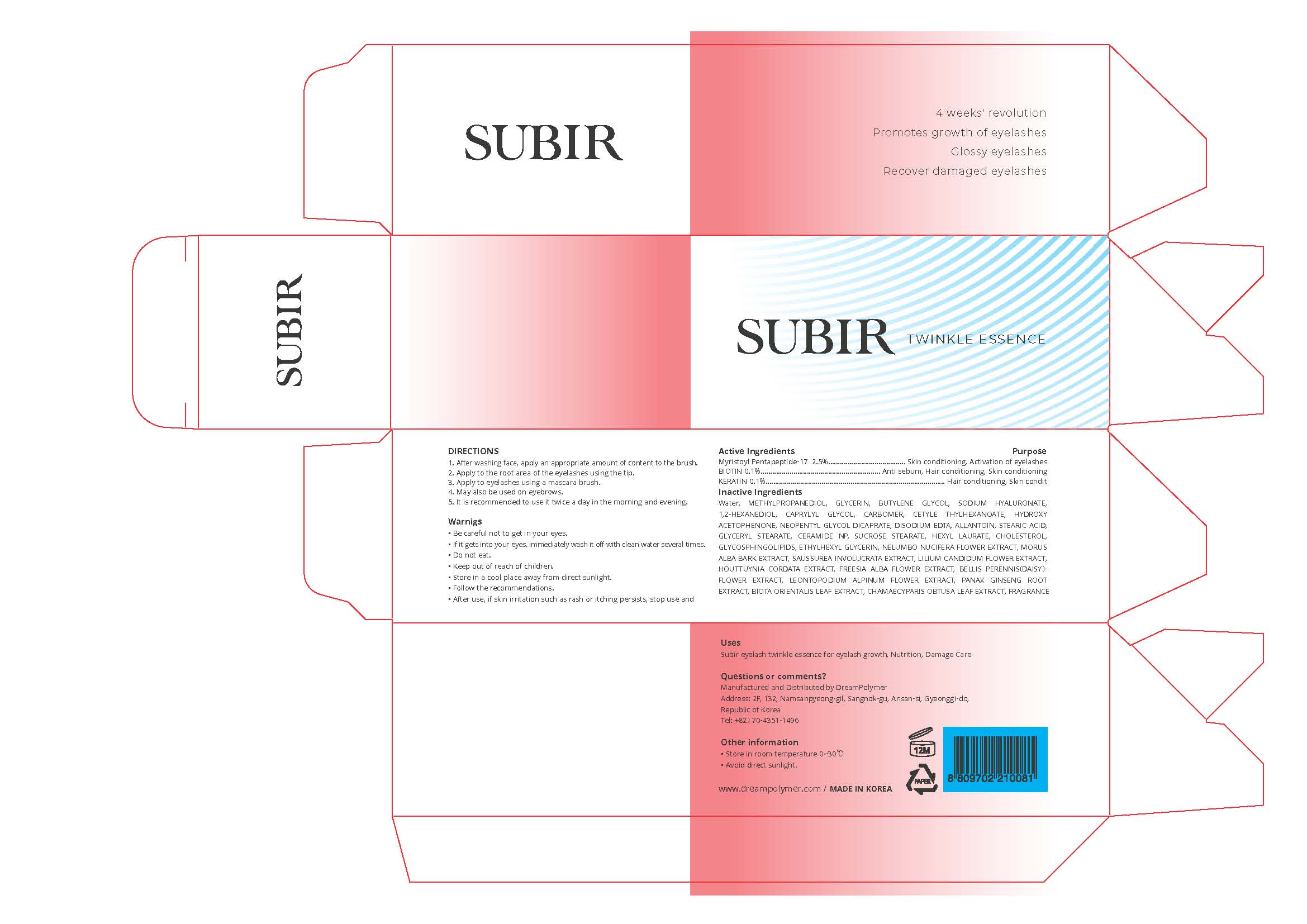 DRUG LABEL: SUBIR
NDC: 81716-006 | Form: CREAM
Manufacturer: Dream Polymer
Category: otc | Type: HUMAN OTC DRUG LABEL
Date: 20210330

ACTIVE INGREDIENTS: BIOTIN 0.1 g/10 g
INACTIVE INGREDIENTS: Water; METHYLPROPANEDIOL; GLYCERIN; BUTYLENE GLYCOL; 1,2-HEXANEDIOL; CAPRYLYL GLYCOL; NEOPENTYL GLYCOL DICAPRATE; ALLANTOIN; STEARIC ACID; CERAMIDE NP; SUCROSE STEARATE; HEXYL LAURATE; CHOLESTEROL

Active Ingredient(s)

Myristoyl Pentapeptide-17 2.5%
BIOTIN 0.1%
KERATIN 0.1%

Purpose

Myristoyl Pentapeptide-17 - Skin conditioning, Activation of eyelashes
BIOTIN 0.1% - Anti sebum, Hair conditioning, Skin conditioning
KERATIN 0.1% - Hair conditioning, Skin conditioning

Use

 Subir eyelash twinkle essence for eyelash growth, Nutrition, Damage Care

Warnings

 Be careful not to get in your eyes.
 If it gets into your eyes, immediately wash if off with clean water several times
 Do not eat.
 Keep out of reach of children.
 Store in a cool place away from direct sunlight.
 Follow the recommendations.
 After use, if skin irritation such as rash or itching persists, stop use

 Keep out of reach of children.

Directions

 After washing face, apply an appropriate amount of content to the brush.
 Apply to the root area of the eyelashes using the tip.
 Apply to eyelashes using a mascara brush.
 May also be used on eyebrows.
 It is recommended to use it twice a day in the morning and evening.

Other information

・ Store in room temperature 0~30℃
・ Avoid direct sunlight.

Inactive ingredients

Water, METHYLPROPANEDIOL, GLYCERIN, BUTYLENE GLYCOL, SODIUM HYALURONATE, 1,2-HEXANEDIOL, CAPRYLYL GLYCOL, CARBOMER, CETYLE THYLHEXANOATE, HYDROXY ACETOPHENONE, NEOPENTYL GLYCOL DICAPRATE, DISODIUM EDTA, ALLANTOIN, STEARIC ACID, GLYCERYL STEARATE, CERAMIDE NP, SUCROSE STEARATE, HEXYL LAURATE, CHOLESTEROL, GLYCOSPHINGOLIPIDS, ETHYLHEXYL GLYCERIN, NELUMBO NUCIFERA FLOWER EXTRACT, MORUS ALBA BARK EXTRACT, SAUSSUREA INVOLUCRATA EXTRACT, LILIUM CANDIDUM FLOWER EXTRACT, HOUTTUYNIA CORDATA EXTRACT, FREESIA ALBA FLOWER EXTRACT, BELLIS PERENNIS(DAISY)FLOWER EXTRACT, LEONTOPODIUM ALPINUM FLOWER EXTRACT, PANAX GINSENG ROOT EXTRACT, BIOTA ORIENTALIS LEAF EXTRACT, CHAMAECYPARIS OBTUSA LEAF EXTRACT, FRAGRANCE